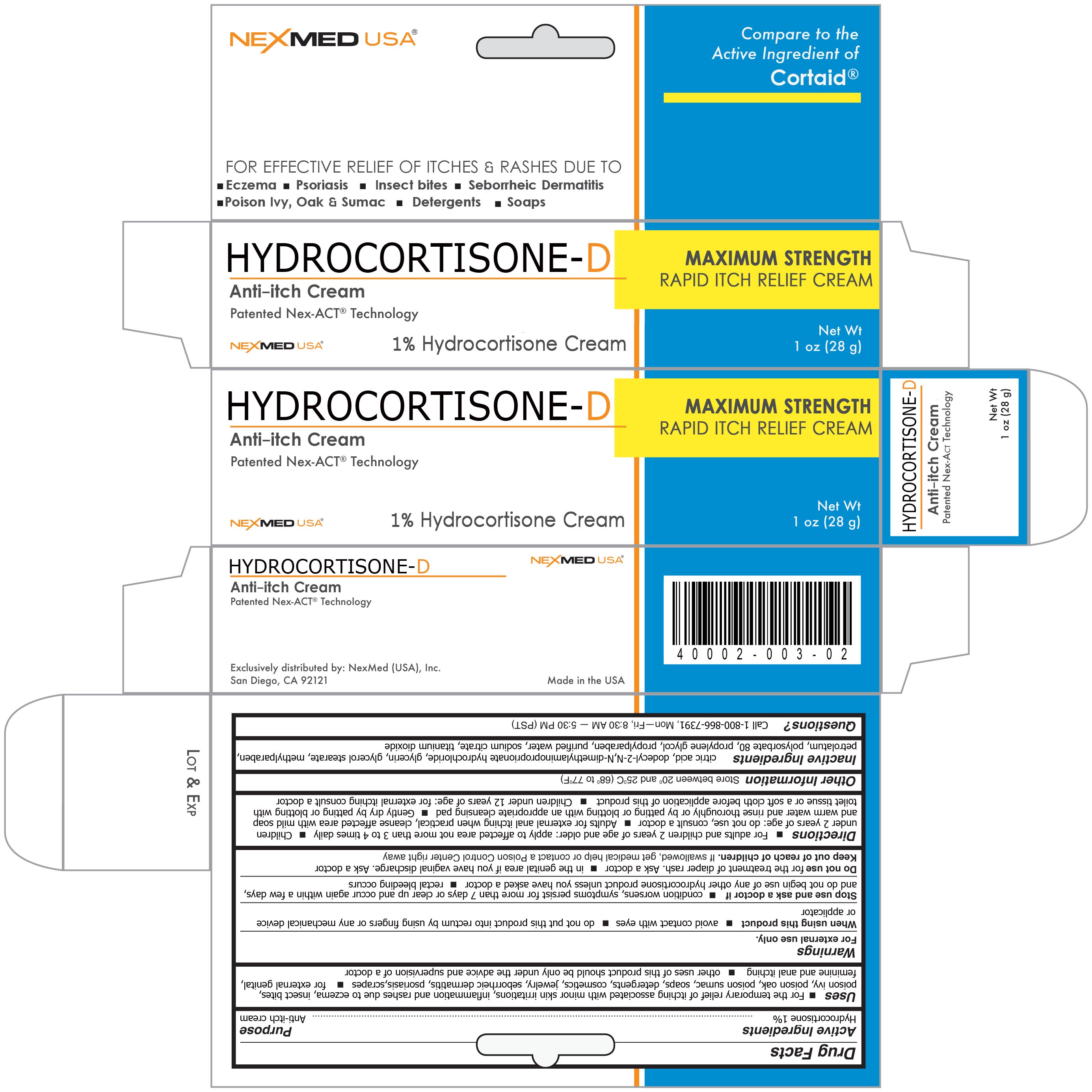 DRUG LABEL: Hydrocortisone
NDC: 40002-003 | Form: CREAM
Manufacturer: NexMed (USA), Inc.
Category: otc | Type: HUMAN OTC DRUG LABEL
Date: 20110819

ACTIVE INGREDIENTS: Hydrocortisone 1 g/100 g
INACTIVE INGREDIENTS: Citric Acid Monohydrate; Dodecyl-2-N,N-Dimethylaminopropionate Hydrochloride; GLYCERIN; GLYCERYL MONOSTEARATE    ; METHYLPARABEN; PETROLATUM; POLYSORBATE 80    ; PROPYLENE GLYCOL    ; PROPYLPARABEN; WATER

Drug Facts

Active Ingredient

Hydrocortisone 1%

Purpose

Anti-itch cream

Uses

- For the temporary relief of itching associated with minor skin irritations, inflammation and rashes due to eczema, insect bites, poison ivy, poison oak, poison sumac, soaps, detergents, cosmetics, jewelry, seborrheic dermatitis, psoriasis, scrapes
- for external genital, feminine and anal itching
- other uses of this product should be only under the advice and supervision of a doctor

Warnings

For external use only.

When using this product

- avoid contact with the eyes
- do not put this product into the rectum by using fingers or any mechanical device or applicator

Stop use and ask a doctor if

- condition worsens, symptoms persist for more than 7 days or clear up and occur again within a few days, and do not begin use of any other hydrocortisone product unless you have asked a doctor
- rectal bleeding occurs

Do not use

- for the treatment of diaper rash. Ask a doctor
- in the genital area if you have vaginal discharge. Ask a doctor

Keep out of reach of children

If swallowed, get medical help or contact a Poison Control Center right away

Directions

- For adults and children 2 years of age and older: apply to affected area not more than 3 to 4 times daily
- Children under 2 years of age: do not use, consult a doctor
- Adults for external anal itching when practical, cleanse the affected area with mild soap and warm water and rinse thoroughly or by patting or blotting with an appropriate cleansing pad
- Gently dry by patting or blotting toilet tissue or a soft cloth before application of this product
- Children under 12 years of age: for external itching consult a doctor

Other information

Store between 20⁰ and 25⁰C (68⁰ to 77⁰F)

Inactive Ingredients

citric acid, dodecyl-2-N N-dimethylaminopropionate hydrochloride, glycerin, glycerol stearate, methylparaben, petrolatum, polysorbate 80, propylene glycol, propylparaben, purified water, sodium citrate, titanium dioxide

Questions?

Call 1-800-866-7391, Mon-Fri, 8:30 AM - 5:30 PM (PST)